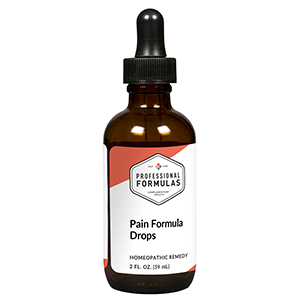 DRUG LABEL: Pain Formula Drops
NDC: 63083-2046 | Form: LIQUID
Manufacturer: Professional Complementary Health Formulas
Category: homeopathic | Type: HUMAN OTC DRUG LABEL
Date: 20190815

ACTIVE INGREDIENTS: GINGER 3 [hp_X]/59 mL; SALIX ALBA BARK 3 [hp_X]/59 mL; ACONITUM NAPELLUS WHOLE 6 [hp_X]/59 mL; ARSENIC TRIOXIDE 6 [hp_X]/59 mL; AMARYLLIS BELLADONNA WHOLE 6 [hp_X]/59 mL; BRYONIA ALBA ROOT 6 [hp_X]/59 mL; CAPSICUM 6 [hp_X]/59 mL; CAUSTICUM 6 [hp_X]/59 mL; CINCHONA OFFICINALIS BARK 6 [hp_X]/59 mL; HYPERICUM PERFORATUM WHOLE 6 [hp_X]/59 mL; TOXICODENDRON PUBESCENS LEAF 6 [hp_X]/59 mL; VITAMIN A 6 [hp_X]/59 mL; ASCORBIC ACID 6 [hp_X]/59 mL; .ALPHA.-TOCOPHEROL 6 [hp_X]/59 mL; ACETAMINOPHEN 6 [hp_X]/59 mL; ASPIRIN 6 [hp_X]/59 mL; IBUPROFEN 6 [hp_X]/59 mL
INACTIVE INGREDIENTS: ALCOHOL; WATER

C46

ACTIVE INGREDIENTS

Zingiber officinale 3X
Salix alba 3X, 6X
Aconitum napellus 6X
Arsenicum album 6X
Belladonna 6X
Bryonia 6X
Capsicum annuum 6X
Causticum 6X
Cinchona officinalis 6X
Hypericum perforatum 6X
Rhus toxicodendron 6X
Vitamin A 6X
Vitamin C 6X
Vitamin E 6X
Acetaminophen 6X, 30X
Aspirin 6X, 30X
Ibuprofen 6X, 30X

QUESTIONS

Professional Formulas

PO Box 2034 Lake Oswego, OR 97035

INDICATIONS

Temporarily relieves minor aches or pains due to overexertion, fatigue, or illness.*

PURPOSE

*Claims based on traditional homeopathic practice, not accepted medical evidence. Not FDA evaluated.

WARNINGS

In case of overdose, get medical help or contact a poison control center right away.

Keep out of the reach of children.

PREGNANCY OR BREAST FEEDING

If pregnant or breastfeeding, ask a healthcare professional before use.

DIRECTIONS

Place drops under tongue 30 minutes before/after meals. Adults and children 12 years and over: Take 10 drops up to 3 times per day for up to 6 weeks. For immediate onset of symptoms, take 10 to 15 drops every 15 minutes up to 3 hours. For less severe symptoms, take 10-15 drops hourly up to 8 hours. Consult a physician for use in children under 12 years of age.

OTHER INFORMATION

Tamper resistant. If seal is broken, do not use. After opening, close container tightly and store at room temperature away from heat.

INACTIVE INGREDIENTS

20% ethanol, purified water.

LABEL

Est 1985

Professional Formulas

Complementary Health

Pain Formula Drops

Homeopathic Remedy

2 FL. OZ. (59 mL)